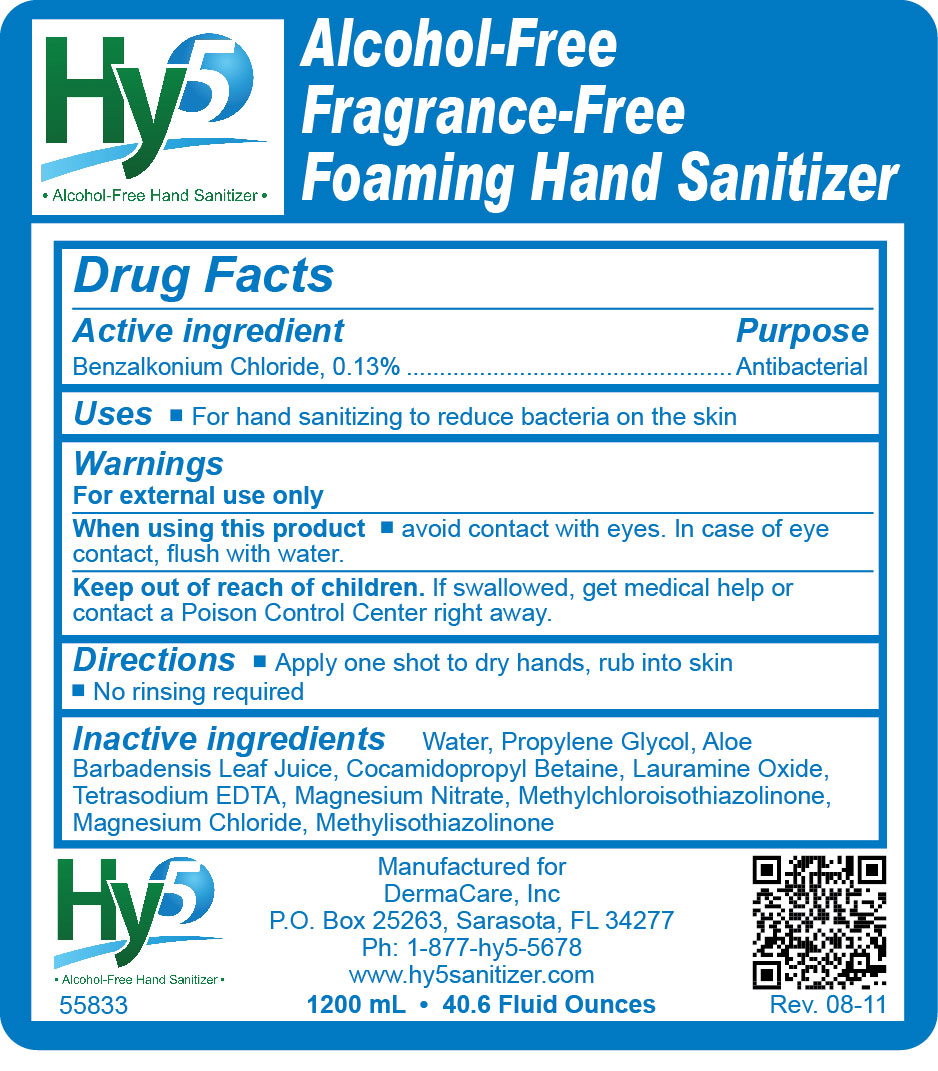 DRUG LABEL: Hy5 Alcohol Free Fragrance Free Foaming Hand Sanitizer
NDC: 11084-138 | Form: LIQUID
Manufacturer: Deb USA, Inc.
Category: otc | Type: HUMAN OTC DRUG LABEL
Date: 20110826

ACTIVE INGREDIENTS: BENZALKONIUM CHLORIDE 0.13 mL/100 mL
INACTIVE INGREDIENTS: WATER; PROPYLENE GLYCOL; ALOE VERA LEAF; COCAMIDOPROPYL BETAINE; LAURAMINE OXIDE; EDETATE SODIUM; METHYLCHLOROISOTHIAZOLINONE; METHYLISOTHIAZOLINONE; MAGNESIUM NITRATE; MAGNESIUM CHLORIDE

Drug Facts

Active ingredient

Benzalkonium Chloride 0.13%

Purpose

Antibacterial

Uses

For hand sanitizing to reduce bacteria on the skin

Warnings

For external use only

When using this product avoid contact with eyes. In case of eye contact, flush with water.

Keep out of reach of children. If swallowed, get medical help or contact a Poison Control Center right away.

Directions

Apply one shot to dry hands, rub into skin

No rinsing required

Inactive ingredients

Water, Propylene Glycol, Aloe Barbadensis Leaf Juice, Cocamidopropyl Betaine, Lauramine Oxide, Tetrasodium EDTA, Magnesium Nitrate, Methylchloroisothiazolinone, Magnesium Chloride, Methylisothiazolinone

PACKAGE LABEL

Hy5 Alcohol Free Hand Sanitizer

Alcohol Free Fragrance Free Foaming Hand Sanitizer

55833

Manufactured for

DermaCare, Inc.

P.O. Box 25263, Sarasota, FL 34277

Ph: 1-877-hy5-5678

www.hy5sanitizer.com

1200 mL 40.6 Fluid Ounces

Rev. 08-11